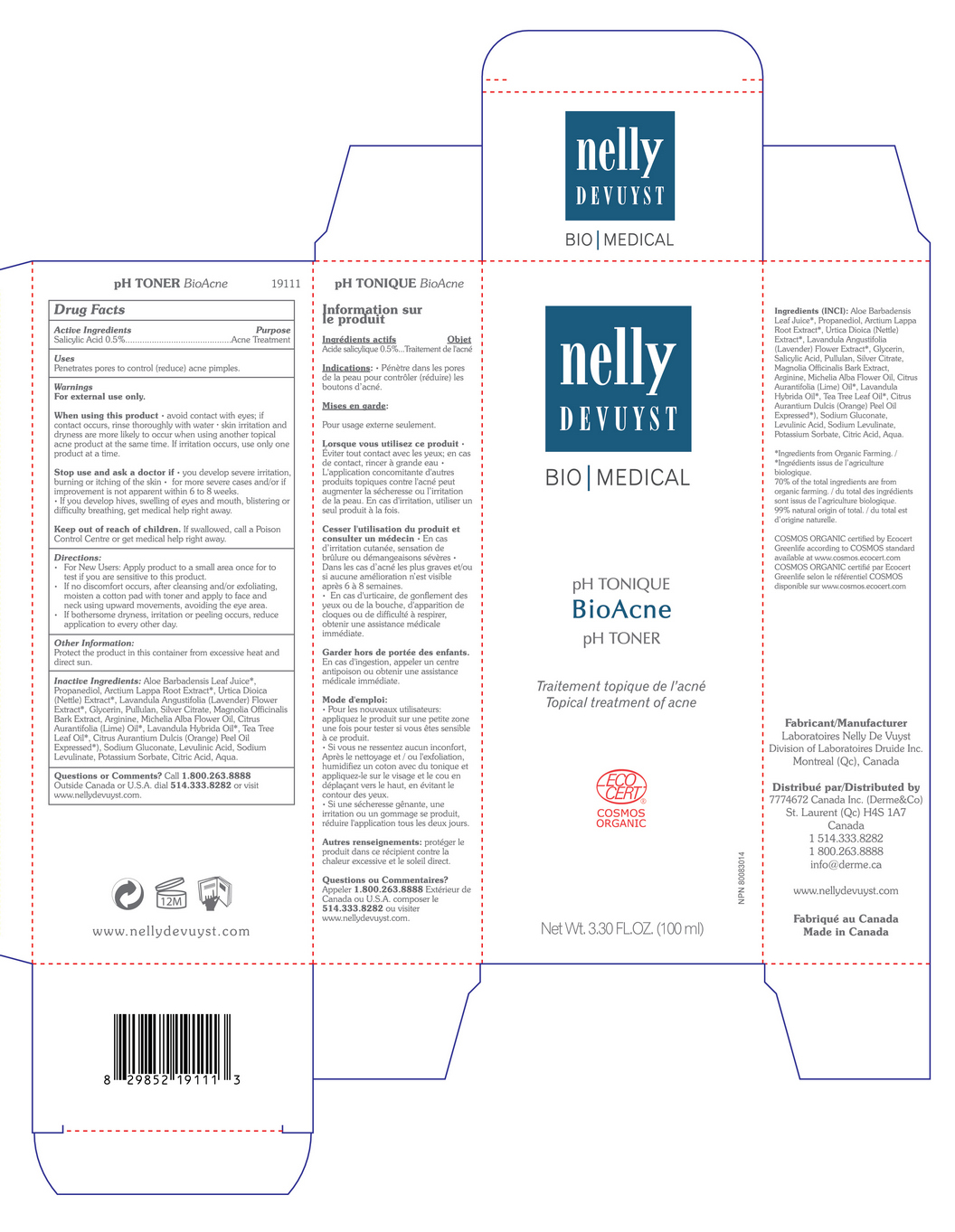 DRUG LABEL: NELLY DEVUYST pH TONER BIOACNE
NDC: 71447-007 | Form: LIQUID
Manufacturer: LABORATOIRES DRUIDE INC
Category: otc | Type: HUMAN OTC DRUG LABEL
Date: 20210101

ACTIVE INGREDIENTS: SALICYLIC ACID 0.5 g/100 mL
INACTIVE INGREDIENTS: ARGININE; MICHELIA ALBA LEAF OIL; LIME OIL; LAVANDIN OIL; CITRUS AURANTIUM FRUIT OIL; SODIUM GLUCONATE; LEVULINIC ACID; POTASSIUM SORBATE; MAGNOLIA OFFICINALIS BARK; GLYCERIN; LAVANDULA ANGUSTIFOLIA FLOWER; CITRIC ACID MONOHYDRATE; SILVER CITRATE; PULLULAN; TEA TREE OIL; ALOE VERA LEAF; PROPANEDIOL; ARCTIUM LAPPA ROOT OIL; URTICA DIOICA LEAF; SODIUM LEVULINATE; WATER

NELLY DEVUYST pH TONER BIOACNE 100mL

Active Ingredients

Salicylic Acid 0.5%

Purpose

Acne Treatment

Uses

Penetrates pores to control or reduce acne pimples.

Warnings

For external use only.

When using this product

▪ avoid contact with eyes. If contact occurs, rinse thoroughly with water ▪ Skin irritation and dryness are more likely to occur when using another topical acne product at the same time. If irritation occurs, use only one product at a time.

and ask a doctor if

▪ you develop severe irritation, burning or itching of the skin ▪ for more severe cases and or if improvement is not apparent within 6 to 8 weeks ▪ If you develop hives, swelling of eyes and mouth, blistering or difficulty breathing, get medical help right away.

Keep out of reach of children

If swallowed, get medical help or contact a Poison Control Center right away.

Directions

▪ For new users: apply product to a small area once to test if you are sensitive to this product.

▪ If no discomfort occurs, after cleansing and or exfoliating, moisten a cotton pad with toner and apply to face and neck using upward movements, avoiding the eye area.

▪ If bothersome dryness, irritation or peeling occurs, reduce application to every other day.

Other Information

Protect the product in this container from excessive heat and direct sun.

Inactive Ingredients

Aloe Barbadensis Leaf Juice*, Propanediol, Arctium Lappa Root Extract*, Urtica Dioica (Nettle) Extract*, Lavandula Angustifolia (Lavender) Flower Extract*, Pullulan, Silver Citrate, Magnolia Officinalis Bark Extract, Arginine, Salicylic Acid, Michelia Alba Flower Oil, Citrus Aurantifolia (Lime) Oil*, Lavandula Hybrida Oil*, Tea Tree Leaf Oil*, Citrus Aurantium Dulcis (Orange) Peel Oil Expressed*, Sodium Gluconate, Levulinic Acid, Sodium Levulinate, Potassium Sorbate, Citric Acid, Aqua.

Certified organic*

Questions or Comments?

+1 800-263-8888

Outside Canada or United States, dial +1 514-333-8282, or visit www.nellydevuyst.com

Distributed By

7774672 Canada Inc (Derme & Co)

4980 Chemin Bois Franc

St. Laurent, QC H4S 1A7

Canada

+1 514-333-8282, +1 800-263-8888

www.nellydevuyst.com

Made in Canada